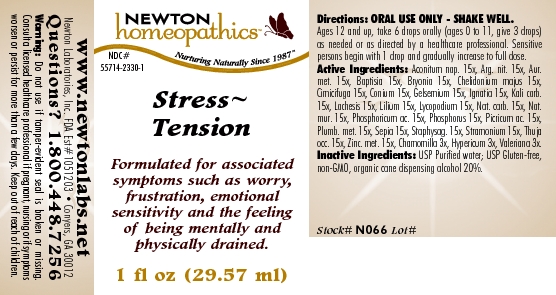 DRUG LABEL: Stress Tension 
NDC: 55714-2330 | Form: LIQUID
Manufacturer: Newton Laboratories, Inc.
Category: homeopathic | Type: HUMAN OTC DRUG LABEL
Date: 20110301

ACTIVE INGREDIENTS: Aconitum Napellus 15 [hp_X]/1 mL; Silver Nitrate 15 [hp_X]/1 mL; Gold 15 [hp_X]/1 mL; Baptisia Tinctoria 15 [hp_X]/1 mL; Bryonia Alba Root 15 [hp_X]/1 mL; Chelidonium Majus 15 [hp_X]/1 mL; Black Cohosh 15 [hp_X]/1 mL; Conium Maculatum Flowering Top 15 [hp_X]/1 mL; Gelsemium Sempervirens Root 15 [hp_X]/1 mL; Strychnos Ignatii Seed 15 [hp_X]/1 mL; Potassium Carbonate 15 [hp_X]/1 mL; Lachesis Muta Venom 15 [hp_X]/1 mL; Lilium Lancifolium Whole Flowering 15 [hp_X]/1 mL; Lycopodium Clavatum Spore 15 [hp_X]/1 mL; Sodium Carbonate 15 [hp_X]/1 mL; Sodium Chloride 15 [hp_X]/1 mL; Phosphoric Acid 15 [hp_X]/1 mL; Phosphorus 15 [hp_X]/1 mL; Trinitrophenol 15 [hp_X]/1 mL; Lead 15 [hp_X]/1 mL; Sepia Officinalis Juice 15 [hp_X]/1 mL; Delphinium Staphisagria Seed 15 [hp_X]/1 mL; Datura Stramonium 15 [hp_X]/1 mL; Thuja Occidentalis Leafy Twig 15 [hp_X]/1 mL; Zinc 15 [hp_X]/1 mL; Matricaria Recutita 3 [hp_X]/1 mL; Hypericum Perforatum 3 [hp_X]/1 mL; Valerian 3 [hp_X]/1 mL
INACTIVE INGREDIENTS: Alcohol

Stress Tension

INDICATIONS & USAGE SECTION

Stress~Tension Formulated for associated symptoms such as worry, frustration, emotional sensitivity and the feeling of being mentally and physically drained.

DOSAGE & ADMINISTRATION SECTION

Directions: ORAL USE ONLY - SHAKE WELL. Ages 12 and up, take 6 drops orally (ages 0 to 11, give 3 drops) as needed or as directed by a healthcare professional. Sensitive persons begin with 1 drop and gradually increase to full dose.

OTC - ACTIVE INGREDIENT SECTION

Aconitum nap. 15x, Arg. nit. 15x, Aur.met. 15x, Baptisia 15x, Bryonia 15x, Chelidonium majus 15x, Cimicifuga 15x, Conium 15x, Gelsemium 15x, Ignatia 15x, Kali carb.15x, Lachesis 15x, Lilium 15x, Lycopodium 15x, Nat. carb. 15x, Nat.mur. 15x, Phosphoricum ac. 15x, Phosphorus 15x, Picricum ac. 15x, Plumb. met. 15x, Sepia 15x, Staphysag. 15x, Stramonium 15x, Thuja occ. 15x, Zinc. met. 15x, Chamomilla 3x, Hypericum 3x, Valeriana 3x.

OTC - PURPOSE SECTION

Formulated for associated symptoms such as worry, frustration, emotional sensitivity and the feeling of being mentally and physically drained.

INACTIVE INGREDIENT SECTION

Inactive Ingredients: USP Purified Water; USP Gluten-free, non-GMO, organic cane dispensing alcohol 20%

QUESTIONS SECTION

www.newtonlabs.net Newton Laboratories, Inc. FDA Est # 1051203 - Conyers, GA 30012
Questions? 1.800.448.7256

WARNINGS SECTION

Warning: Do not use if tamper - evident seal is broken or missing. Consult a licensed healthcare professional if pregnant, nursing or if symptoms worsen or persist for more than a few days. Keep out of reach of children.

OTC - PREGNANCY OR BREAST FEEDING SECTION

Consult a licensed healthcare professional if pregnant, nursing or if symptoms worsen or persist for more than a few days.

OTC - KEEP OUT OF REACH OF CHILDREN SECTION

Keep out of reach of children.